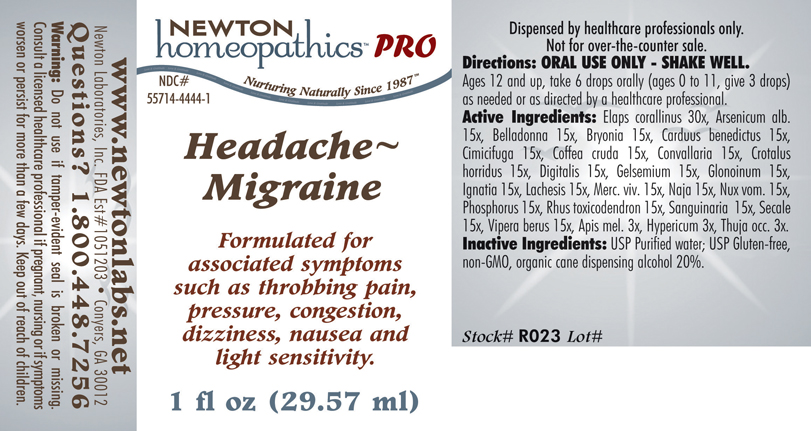 DRUG LABEL: Headache - Migraine 
NDC: 55714-4444 | Form: LIQUID
Manufacturer: Newton Laboratories, Inc.
Category: homeopathic | Type: HUMAN PRESCRIPTION DRUG LABEL
Date: 20110601

ACTIVE INGREDIENTS: Micrurus Corallinus Venom 30 [hp_X]/1 mL; Arsenic Trioxide 15 [hp_X]/1 mL; Atropa Belladonna 15 [hp_X]/1 mL; Bryonia Alba Root 15 [hp_X]/1 mL; Centaurea Benedicta 15 [hp_X]/1 mL; Black Cohosh 15 [hp_X]/1 mL; Arabica Coffee Bean 15 [hp_X]/1 mL; Convallaria Majalis 15 [hp_X]/1 mL; Crotalus Horridus Horridus Venom 15 [hp_X]/1 mL; Digitalis 15 [hp_X]/1 mL; Gelsemium Sempervirens Root 15 [hp_X]/1 mL; Nitroglycerin 15 [hp_X]/1 mL; Strychnos Ignatii Seed 15 [hp_X]/1 mL; Lachesis Muta Venom 15 [hp_X]/1 mL; Mercury 15 [hp_X]/1 mL; Naja Naja Venom 15 [hp_X]/1 mL; Strychnos Nux-vomica Seed 15 [hp_X]/1 mL; Phosphorus 15 [hp_X]/1 mL; Toxicodendron Pubescens Leaf 15 [hp_X]/1 mL; Sanguinaria Canadensis Root 15 [hp_X]/1 mL; Claviceps Purpurea Sclerotium 15 [hp_X]/1 mL; Vipera Berus Venom 15 [hp_X]/1 mL; Apis Mellifera 3 [hp_X]/1 mL; Hypericum Perforatum 3 [hp_X]/1 mL; Thuja Occidentalis Leafy Twig 3 [hp_X]/1 mL
INACTIVE INGREDIENTS: Alcohol

Headache - Migraine

INDICATIONS & USAGE SECTION

HEADACHE - MIGRAINE Formulated for associated symptoms such as throbbing pain, pressure, congestion, dizziness, nausea and light sensitivity.

DOSAGE & ADMINISTRATION SECTION

Directions: ORAL USE ONLY - SHAKE WELL. Ages 12 and up, take 6 drops orally (ages 0 to 11, give 3 drops) as needed or as directed by a healthcare professional.

ACTIVE INGREDIENT SECTION

Elaps corallinus 30x, Arsenicum alb. 15x, Belladonna 15x, Bryonia 15x, Carduus benedictus 15x, Cimicifuga 15x, Coffea cruda 15x, Convallaria 15x, Crotalus horridus 15x, Digitalis 15x, Gelsemium 15x, Glonoinum 15x, Ignatia 15x, Lachesis 15x, Merc. viv. 15x, Naja 15x, Nux vom. 15x, Phosphorus 15x, Rhus toxicodendron 15x, Sanguinaria 15x, Secale 15x, Vipera berus 15x, Apis mel. 3x, Hypericum 3x, Thuja occ. 3x.

PURPOSE SECTION

Formulated for associated symptoms such as throbbing pain, pressure, congestion, dizziness, nausea and light sensitivity.

INACTIVE INGREDIENT SECTION

Inactive Ingredients: USP Purified Water; USP Gluten-free, non-GMO, organic cane dispensing alcohol 20%.

QUESTIONS? SECTION

www.newtonlabs.net Newton Laboratories, Inc. FDA Est # 1051203 - Conyers, GA 30012
Questions? 1.800.448.7256

WARNINGS SECTION

Warning: Do not use if tamper - evident seal is broken or missing. Consult a licensed healthcare professional if pregnant, nursing or if symptoms worsen or persist for more than a few days. Keep out of reach of children.

PREGNANCY OR BREAST FEEDING SECTION

Consult a licensed healthcare professional if pregnant or nursing or if symptoms worsen or persist for more than a few days.

KEEP OUT OF REACH OF CHILDREN SECTION

Keep out of reach of children.